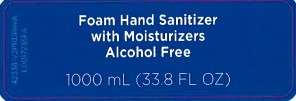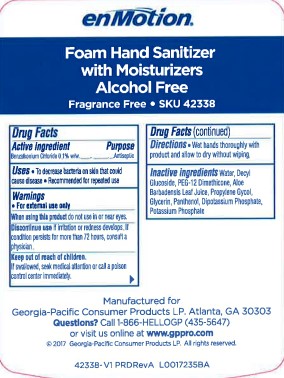 DRUG LABEL: Hand Sanitizer
NDC: 54622-148 | Form: LIQUID
Manufacturer: Georgia-Pacific Consumer Products LP 
Category: otc | Type: HUMAN OTC DRUG LABEL
Date: 20260204

ACTIVE INGREDIENTS: BENZALKONIUM CHLORIDE 1 mg/1 mL
INACTIVE INGREDIENTS: WATER; DECYL GLUCOSIDE; PEG-12 DIMETHICONE; ALOE VERA LEAF; PROPYLENE GLYCOL; GLYCERIN; PANTHENOL; DIBASIC POTASSIUM PHOSPHATE; POTASSIUM PHOSPHATE, UNSPECIFIED FORM

enMotion 148.000/148AA
Alcohol Free Hand Sanitizer

Claims

enMotion

Foam Hand Sanitizer

with Moisturizers

Alcohol Free

Fregrance Free SKU 42338

Active ingredient

Benzalkonium Chloride 0.1% w/w

Purpose

Antiseptic

Uses

- To decrease bacteria on skin that could cause disease
- Recommended for repeated use

Warnings

for external use only

When using this product

do not use in or near eyes.

Discontinue use

If irritation or redness develops. If condition persists for more than 72 hours, consult a physician.

Keep out of reach of children.

If swallowed, seek medical attention or call a poison control center immediately.

Directions

- Wet hands thoroughly with product and allow to dry without wiping.

Inactive ingredients

water, decyl glucoside, PEG-12 Dimethicone, Aloe Barbadensis Leaf Juice, Propylene Gycol, Glycerin, Panthenol, Dipotassium Phosphate, Potassium Phosphate

Adverse Reaction

Manufactured for

Georgia-Pacific Consumer Products LP. Altanta, GA 30303

Questions? Call 1-866-HELLOGP (435-5647)

or visit us online at www.gppro.com

2017 Georgia-Pacific Consumer Products LP All rights reserved

Principal display panel

Foam Hand Sanitizer

with Moisturizers

Alcohol Free

1000 mL (33.8 FL OZ)